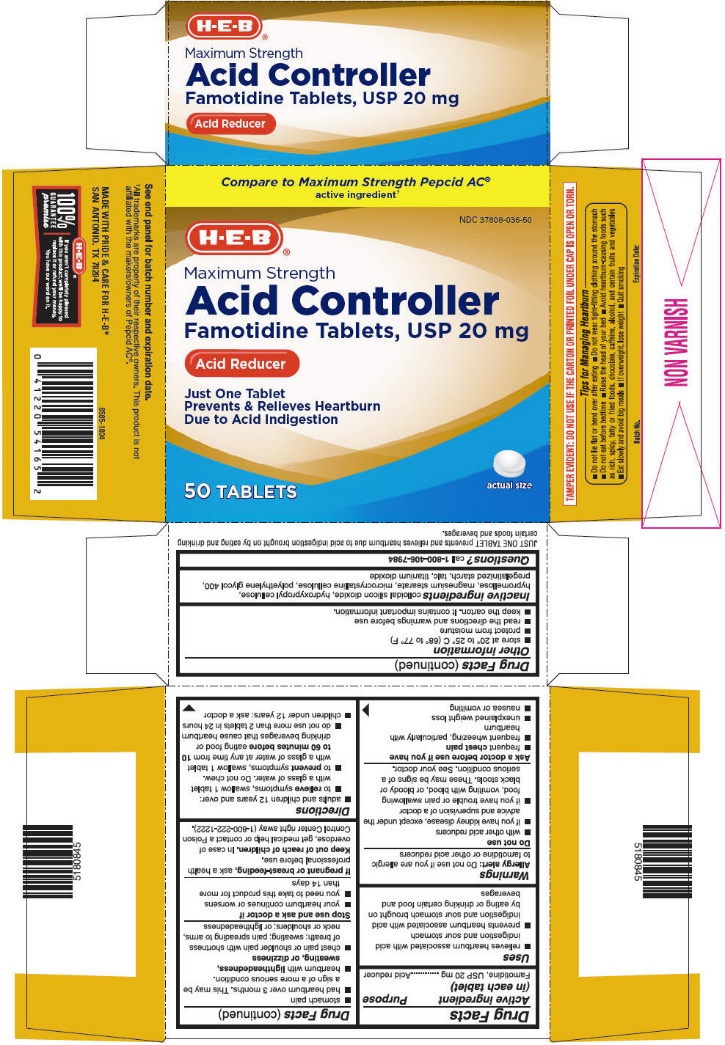 DRUG LABEL: Famotidine
NDC: 37808-036 | Form: TABLET, FILM COATED
Manufacturer: HEB
Category: otc | Type: HUMAN OTC DRUG LABEL
Date: 20181207

ACTIVE INGREDIENTS: FAMOTIDINE 20 mg/1 1
INACTIVE INGREDIENTS: SILICON DIOXIDE; HYDROXYPROPYL CELLULOSE (1200000 MW); HYPROMELLOSE, UNSPECIFIED; MAGNESIUM STEARATE; MICROCRYSTALLINE CELLULOSE; POLYETHYLENE GLYCOL, UNSPECIFIED; STARCH, CORN; TALC; TITANIUM DIOXIDE

Drug Facts

ACTIVE INGREDIENT (IN EACH TABLET)

Famotidine, USP 20 mg

PURPOSE

Acid reducer

USES

- relieves heartburn associated with acid indigestion and sour stomach
- prevents heartburn associated with acid indigestion and sour stomach brought on by eating or drinking certain food and beverages

WARNINGS

Allergy alert: Do not use if you are allergic to famotidine or other acid reducers

Do not use

- with other acid reducers
- if you have kidney disease, except under the advice and supervision of a doctor
- if you have trouble or pain swallowing food, vomiting with blood, or bloody or black stools. These may be signs of a serious condition. See your doctor.

Ask a doctor before use if you have

- frequent chest pain
- frequent wheezing, particularly with heartburn
- unexplained weight loss
- nausea or vomiting
- stomach pain
- had heartburn over 3 months. This may be a sign of a more serious condition.
- heartburn with lightheadedness, sweating, or dizziness
- chest pain or shoulder pain with shortness of breath; sweating; pain spreading to arms, neck or shoulders; or lightheadedness

Stop use and ask a doctor if

- your heartburn continues or worsens
- you need to take this product for more than 14 days

If pregnant or breast-feeding,

Ask a health professional before use.

Keep out of reach of children.

In case of overdose, get medical help or contact a Poison Control Center right away (1-800-222-1222).

DIRECTIONS

- adults and children 12 years and over:
  - to relieve symptoms, swallow 1 tablet with a glass of water. Do not chew.
  - to prevent symptoms, swallow 1 tablet with a glass of water at any time from 10 to 60 minutes before eating food or drinking beverages that cause heartburn
  - do not use more than 2 tablets in 24 hours
- children under 12 years: ask a doctor

OTHER INFORMATION

- store at 20° to 25°C (68° to 77°F)
- protect from moisture
- read the directions and warnings before use
- keep the carton. It contains important information.

INACTIVE INGREDIENTS

Colloidal silicon dioxide, hydroxypropyl cellulose, hypromellose, magnesium stearate, microcrystalline cellulose, polyethylene glycol 400, pregelatinized starch, talc, titanium dioxide

QUESTIONS?

Call 1-800-406-7984

PATIENT INFORMATION

- JUST ONE TABLET prevents and relieves heartburn due to acid indigestion brought on by eating and drinking certain foods and beverages.
- TAMPER EVIDENT: DO NOT USE IF THE CARTON OR PRINTED FOIL UNDER CAP IS OPEN OR TORN.

Tips for Managing Heartburn

- Do not lie flat or bend over after eating
- Do not wear tight-fitting clothing around the stomach
- Do not eat before bedtime
- Raise the head of your bed
- Avoid heartburn-causing foods such as rich, spicy, fatty or fried foods, chocolate, caffeine, alcohol, and certain fruits and vegetables
- Eat slowly and avoid big meals
- If overweight, lose weight
- Quit smoking

PRINCIPAL DISPLAY PANEL - 20 mg Tablet Bottle Carton

Compare to Maximum Strength Pepcid AC®
active ingredient†

NDC 37808-036-50

H-E-B®

Maximum Strength
Acid Controller
Famotidine Tablets, USP 20 mg

Acid Reducer

Just One Tablet
Prevents & Relieves Heartburn
Due to Acid Indigestion

actual size

50 TABLETS